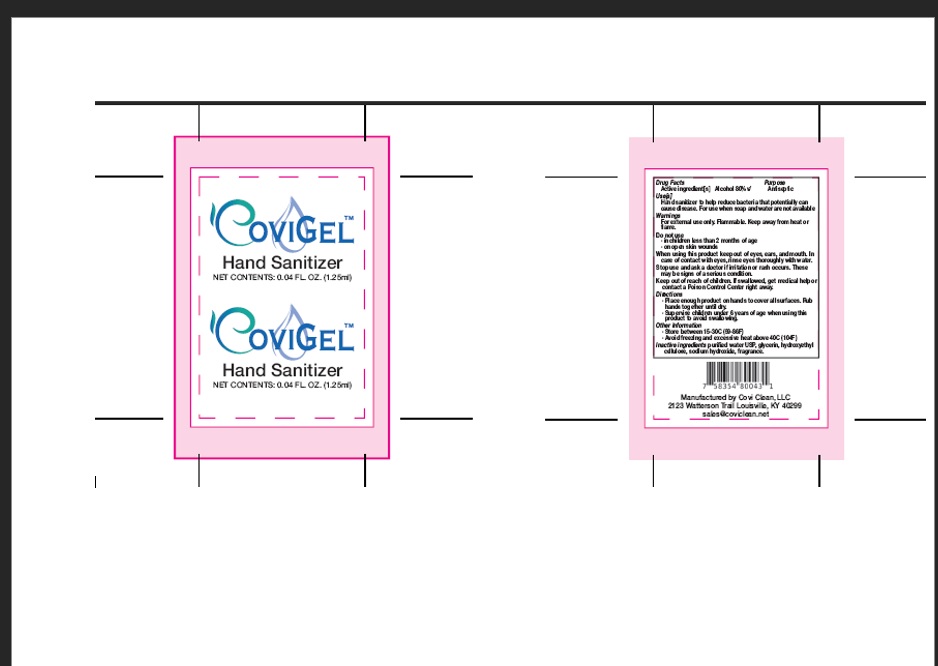 DRUG LABEL: CoviGel
NDC: 74593-003 | Form: LIQUID
Manufacturer: Flavorcraft Industries Inc
Category: otc | Type: HUMAN OTC DRUG LABEL
Date: 20200624

ACTIVE INGREDIENTS: ALCOHOL 80 mL/100 mL
INACTIVE INGREDIENTS: SODIUM HYDROXIDE 0.03 mL/100 mL; HYDROXYETHYL CELLULOSE, UNSPECIFIED 0.97 mL/100 mL; GLYCERIN 1.2 mL/100 mL; WATER 17.85 mL/100 mL

CoviGel Hand Sanitizer 1.25ml

This is a gel hand sanitizer manufactured using only United States Pharmacopoeia (USP) grade ingredients in the preparation of the product.

Active Ingredient(s)

Alcohol 80% v/v.

Purpose

Purpose: Antiseptic

Use

Hand Sanitizer to help reduce bacteria that potentially can cause disease. For use when soap and water are not available.

Warnings

For external use only. Flammable. Keep away from heat or flame

Do not use

- in children less than 2 months of age
- on open skin wounds

When using this product keep out of eyes, ears, and mouth. In case of contact with eyes, rinse eyes thoroughly with water.

Stop use and ask a doctor if irritation or rash occurs. These may be signs of a serious condition.

Keep out of reach of children. If swallowed, get medical help or contact a Poison Control Center right away.

Directions

- Place enough product on hands to cover all surfaces. Rub hands together until dry.
- Supervise children under 6 years of age when using this product to avoid swallowing.

Other information

- Store between 15-30C (59-86F)
- Avoid freezing and excessive heat above 40C (104F)

Inactive ingredients

purified water USP, glycerin, hydroxyethl cellulose, sodium hydroxide, fragrance.

CoviClean 1.25ml

1.25ml NDC, 74593-003-01